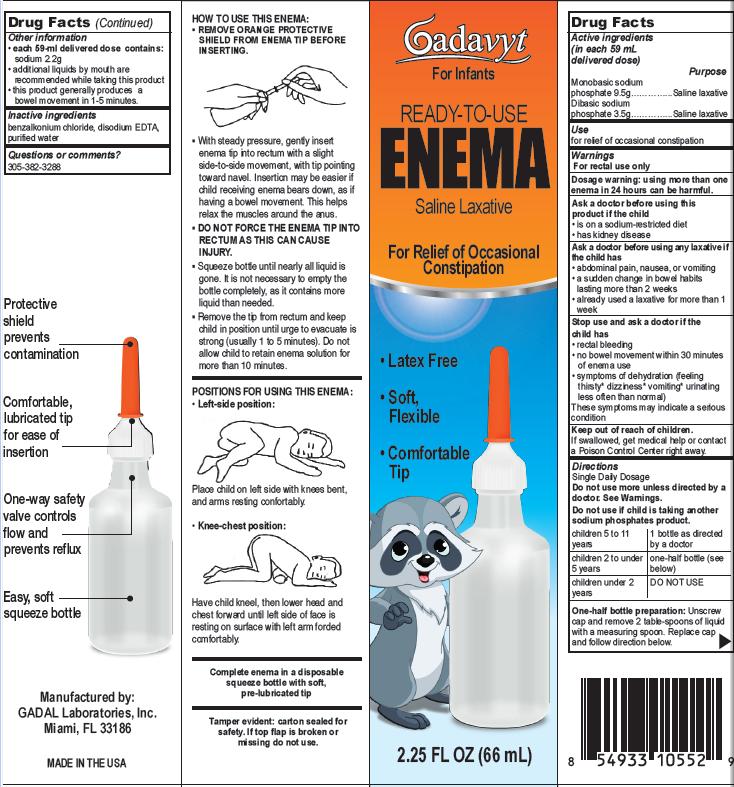 DRUG LABEL: Gadavyt Enema
NDC: 53113-105 | Form: LIQUID
Manufacturer: Gadal Laboratories Inc
Category: otc | Type: HUMAN OTC DRUG LABEL
Date: 20121031

ACTIVE INGREDIENTS: SODIUM PHOSPHATE, DIBASIC 3.5 g/59 mL; SODIUM PHOSPHATE, MONOBASIC 9.5 g/59 mL
INACTIVE INGREDIENTS: BENZALKONIUM CHLORIDE; EDETATE DISODIUM; WATER

Drug Facts

Active ingredients (in each 59 mL delivered dose)

Dibasic sodium phosphate 3.5 g............. Saline Laxative

Monobasic sodium phosphate 9.5 g......... Saline Laxative

Uses
for relief of occasional constipation

Warnings

For rectal use only

Dosage warning: Using more than one enema in 24 hours can be harmful.

Ask a doctor before using this product if the child

- is on a sodium-restricted diet
- has kidney disease

Ask a doctor before using any laxative if the child has

- abdominal pain, nausea or vomiting
- a sudden change in bowel habits that lasting more than 2 weeks
- already used a laxative for more than 1 week

Stop use and ask a doctor if the child has

- rectal bleeding
- no bowel movement within 30 minutes of enema use
- symptoms of dehydration (feeling thirsty, dizziness, vomiting, urinating less often than normal)

These symptoms may indicate a serious condition

If pregnant or breast-feeding,

ask a health professional before use.

Keep out of reach of children.

If swallowed, get medical help or contact a Poison Control Center right away. (1-800-222-1222)

Directions

Single Daily Dosage

Do not use more unless directed by a doctor. See Warnings

Do not use if child is taking another sodium phosphates product.

children 5 to 11 | one bottle as directed by a doctor
children 2 to under 5 years | one-half bottle (see below)
children under 2 years | DO NOT USE

One-half bottle preparation:Unscrew cap and remove 2 table spoons of liquid with a measuring spoon. Replace cap and follow directions below.

Other information

- each 59 mL delivered dose contains: sodium 2.2 g
- additional liquids by mouth are recommended while taking this product
- this product generally produces bowel movement in 1 to 5 minutes

Inactive ingredients

benzalkonium chloride, disodium EDTA, purified water

Questions or comments?

305-382-3288